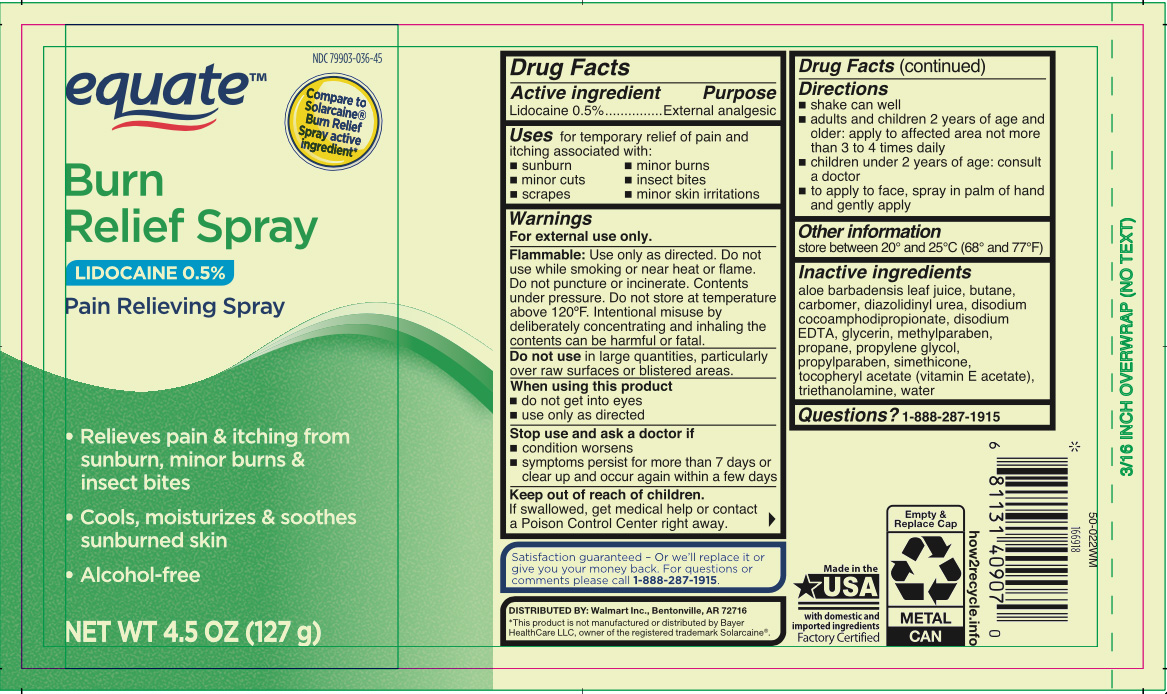 DRUG LABEL: Burn Relief
NDC: 79903-036 | Form: AEROSOL, SPRAY
Manufacturer: WALMART INC.
Category: otc | Type: HUMAN OTC DRUG LABEL
Date: 20260204

ACTIVE INGREDIENTS: LIDOCAINE 0.5 g/100 g
INACTIVE INGREDIENTS: PROPYLPARABEN; BUTANE; DIAZOLIDINYL UREA; PROPYLENE GLYCOL; DIMETHICONE; WATER; EDETATE DISODIUM; GLYCERIN; ALOE VERA LEAF; .ALPHA.-TOCOPHEROL ACETATE; TRIETHANOLAMINE; CARBOMER 940; DISODIUM COCOAMPHODIPROPIONATE; METHYLPARABEN; PROPANE

Equate Burn Relief Spray

Active ingredient

Lidocaine 0.5%

Purpose

External analgesic

Uses

for temporary relief of pain and itching associated with:

- sunburn
- minor cuts
- scrapes
- minor burns
- insect bites
- minor skin irritations

Warnings

For external use only.

Flammable:

Use only as directed. Do not use while smoking or near heat or flame. Do not puncture or incinerate. Contents under pressure. Do not store at temperature above 120°F. Intentional misuse by deliberately concentrating and inhaling the contents can be harmful or fatal.

Do not use

In large quantities, particularly over raw surfaces or blistered areas.

When using this product

- do not get into eyes
- use only as directed

Stop use and ask a doctor if

- condition worsens
- symptoms persist for more than 7 days or clear up and occur again within a few days

Keep out of reach of children.

If swallowed, get medical help or contact a Poison Control Center right away.

Directions

- shake can well
- adults and children 2 years of age and older: apply to affected area not more than 3 to 4 times daily
- children under 2 years of age: consult a doctor
- to apply to face, spray in palm of hand and gently apply

Other information

store between 20°C to 25°C (68° to 77°F)

Inactive ingredients

aloe barbadensis leaf juice, butane, carbomer, diazolidinyl urea, disodium, cocoamphodipropionate, disodium EDTA, glycerin, methylparaben, propane, propylene glycol, propylparaben, simethicone, tocopheryl acetate (vitamin E acetate), triethanolamine, water

Questions?

Call 1-888-287-1915

Principal Display Panel

equate

Burn

Relief Spray

Lidocaine 0.5%

Pain Relieving Spray

- Relieves pain & itching from

sunburn, minor burns &

insect bites

- Cools, moisturizes & soothes

sunburned skin

- Alcohol-free

NET WT 4.5 OZ (127 g)